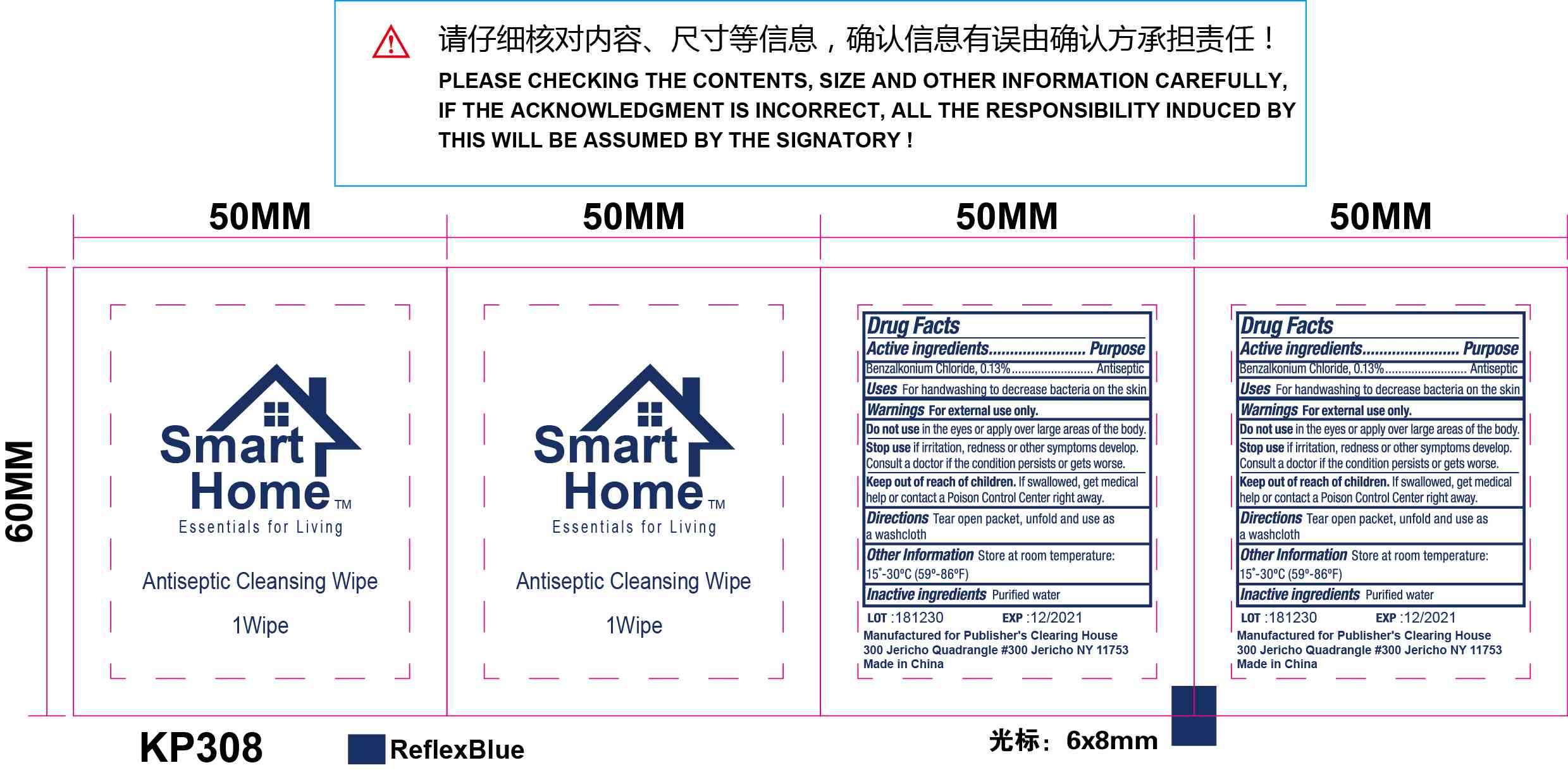 DRUG LABEL: Antiseptic Cleansing Wipe
NDC: 72885-001 | Form: SWAB
Manufacturer: Rudder Int'l Trading (Shanghai) Co., Ltd.
Category: otc | Type: HUMAN OTC DRUG LABEL
Date: 20190215

ACTIVE INGREDIENTS: BENZALKONIUM CHLORIDE 0.13 g/100 g
INACTIVE INGREDIENTS: WATER 99.87 g/100 g

Active ingredients Benzalkonium chloride 0.13%